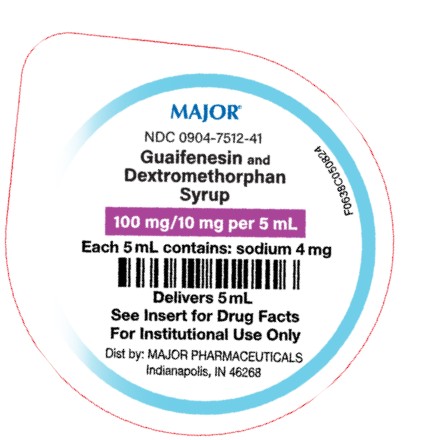 DRUG LABEL: Guaifenesin and Dextromethorphan
NDC: 0904-7512 | Form: SYRUP
Manufacturer: Major Pharmaceuticals
Category: otc | Type: HUMAN OTC DRUG LABEL
Date: 20250129

ACTIVE INGREDIENTS: GUAIFENESIN 100 mg/5 mL; DEXTROMETHORPHAN HYDROBROMIDE 10 mg/5 mL
INACTIVE INGREDIENTS: ANHYDROUS CITRIC ACID; FD&C RED NO. 40; MENTHOL; GLYCERIN; WATER; SACCHARIN SODIUM; SUCROSE; SODIUM BENZOATE; SODIUM CITRATE

Guaifenesin Syrup and Dextromethorphan
Syrup
Expectorant/Cough Suppressant

Active ingredient (in each 5 mL cup) Purpose

Guaifenesin 100 mg .............................................................................................................................. Expectorant
Dextromethorphan hydrobromide 10 mg ............................................................................................ Cough Suppressant

Uses

• helps loosen phlegm (mucus) and thin bronchial secretions to make coughs more productive.
• temporarily relieves cough due to minor throat and bronchial irritation as may occur with a cold.

Warnings

Do not use

if you are now taking a prescription monoamine oxidase inhibitor (MAOI) (certain drugs for depression, psychiatric, or emotional conditions, or Parkinson's disease), or for 2 weeks after stopping the MAOI drug. If you do not know if your prescription drug contains an MAOI, ask a doctor or pharmacist before taking this product.

Ask a doctor before use if you have

• cough that occurs with too much phlegm (mucus)
• cough that lasts or is chronic such as occurs with smoking, asthma, chronic bronchitis or emphysema

Stop use and ask a doctor if

 cough lasts more than 7 days, comes back, or is accompanied by fever, rash, or persistent headache. These could be signs of a serious condition.

If pregnant or breast-feeding,

ask a health professional before use

Keep out of reach of children.

In case of overdose, get medical help or contact a Poison Control Center right away (1-800-222-1222)

Directions

Follow dosage below or use as directed by a physician.
 do not take more than 6 doses in any 24-hour period.
 single use cup. Dose only with cup provided.
 each cup delivers 5 mL
 mL = Milliliter

Age (yr) | Dose (mL)
adults and children 12 years and over | 10 mL every 4 hours
children 6 years to under 12 years | 5 mL every 4 hours
children under 6 years of age | ask a doctor

Other information

 Each 5 mL contains: sodium 4 mg.
 Store at 20° to 25°C (68° to 77°F). Protect from light.

Inactive ingredients:

anhydrous citric acid, FD&C Red No. 40, flavor, glycerin, menthol, purified water, sodium benzoate, sodium citrate dihydrate, sodium saccharin, sucrose.

Questions or comments?

Call1-800-845-8210

How Supplied

- Guaifenesin and Dextromethorphan Syrup is a red, cherry flavored syrup and is available in the following dosage form:
  NDC 0904-7512-41: 5 mL unit dose cup, in a tray of ten cups.

Professional Note: Guaifenesin has been shown to produce a color interference with certain clinical laboratory determinations of 5-hydroxyindoleacetic acid (5-HIAA) and vanillylmandelic acid (VMA).

R10/24

Distributed by:

MAJOR® PHARMACEUTICALS
Indianapolis, IN 46268

PRINCIPAL DISPLAY PANEL - 5 mL Unit Dose Cup Label

Delivers 5 mL
NDC 0904-7512-41

GUAIFENESIN and DEXTROMETHORPHAN
Syrup

100 mg/10 mg per 5 mL

See Insert for Drug Facts
For Institutional Use Only